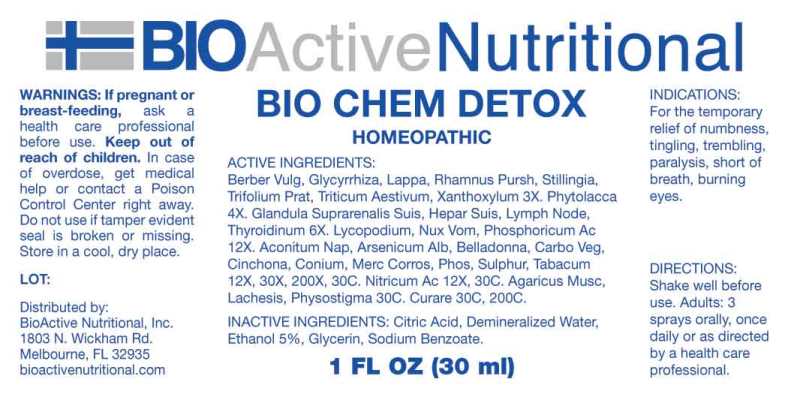 DRUG LABEL: Bio Chem Detox
NDC: 43857-0613 | Form: SPRAY
Manufacturer: BioActive Nutritional, Inc.
Category: homeopathic | Type: HUMAN OTC DRUG LABEL
Date: 20230606

ACTIVE INGREDIENTS: BERBERIS VULGARIS ROOT BARK 3 [hp_X]/1 mL; GLYCYRRHIZA GLABRA 3 [hp_X]/1 mL; ARCTIUM LAPPA ROOT 3 [hp_X]/1 mL; FRANGULA PURSHIANA BARK 3 [hp_X]/1 mL; STILLINGIA SYLVATICA ROOT 3 [hp_X]/1 mL; TRIFOLIUM PRATENSE FLOWER 3 [hp_X]/1 mL; TRITICUM AESTIVUM WHOLE 3 [hp_X]/1 mL; ZANTHOXYLUM AMERICANUM BARK 3 [hp_X]/1 mL; PHYTOLACCA AMERICANA ROOT 4 [hp_X]/1 mL; SUS SCROFA ADRENAL GLAND 6 [hp_X]/1 mL; PORK LIVER 6 [hp_X]/1 mL; SUS SCROFA LYMPH 6 [hp_X]/1 mL; SUS SCROFA THYROID 6 [hp_X]/1 mL; LYCOPODIUM CLAVATUM SPORE 12 [hp_X]/1 mL; STRYCHNOS NUX-VOMICA SEED 12 [hp_X]/1 mL; PHOSPHORIC ACID 12 [hp_X]/1 mL; ACONITUM NAPELLUS WHOLE 12 [hp_X]/1 mL; ARSENIC TRIOXIDE 12 [hp_X]/1 mL; ATROPA BELLADONNA 12 [hp_X]/1 mL; ACTIVATED CHARCOAL 12 [hp_X]/1 mL; CINCHONA OFFICINALIS BARK 12 [hp_X]/1 mL; CONIUM MACULATUM FLOWERING TOP 12 [hp_X]/1 mL; MERCURIC CHLORIDE 12 [hp_X]/1 mL; PHOSPHORUS 12 [hp_X]/1 mL; SULFUR 12 [hp_X]/1 mL; TOBACCO LEAF 12 [hp_X]/1 mL; NITRIC ACID 12 [hp_X]/1 mL; AMANITA MUSCARIA FRUITING BODY 30 [hp_C]/1 mL; LACHESIS MUTA VENOM 30 [hp_C]/1 mL; PHYSOSTIGMA VENENOSUM SEED 30 [hp_C]/1 mL; TUBOCURARINE CHLORIDE 30 [hp_C]/1 mL
INACTIVE INGREDIENTS: CITRIC ACID MONOHYDRATE; GLYCERIN; SODIUM BENZOATE; WATER; ALCOHOL

DRUG FACTS:

ACTIVE INGREDIENTS:

Berberis Vulgaris 3X, Glycyrrhiza Glabra 3X, Lappa Major 3X, Rhamnus Purshiana 3X, Stillingia Sylvatica 3X, Trifolium Pratense 3X, Triticum Aestivum 3X, Xanthoxylum Fraxineum 3X, Phytolacca Decandra 4X, Glandula Suprarenalis Suis 6X, Hepar Suis 6X, Lymph Node (Suis) 6X, Thyroidinum (Suis) 6X, Lycopodium Clavatum 12X, Nux Vomica 12X, Phosphoricum Acidum 12X, Aconitum Napellus 12X, 30X, 200X, 30C, Arsenicum Album 12X,30X, 200X, 30C, Belladonna 12X, 30X, 200X, 30C, Carbo Vegetabilis 12X, 30X, 200X, 30C, Cinchona Officinalis 12X, 30X, 200X, 30C, Conium Maculatum 12X, 30X, 200X, 30C, Mercurius Corrosivus 12X, 30X, 200X, 30C, Phosphorus 12X, 30X, 200X, 30C, Sulphur 12X, 30X, 200X, 30C, Tabacum 12X, 30X, 200X, 30C, Nitricum Acidum 12X, 30C, Agaricus Muscarius 30C, Lachesis Mutus 30C, Physostigma Venenosum 30C, Curare 30C, 200C.

INDICATIONS:

For the temporary relief of numbness, tingling, trembling, paralysis, short of breath, burning eyes.

WARNINGS:

If pregnant or breast-feeding, ask a health care professional before use.

Keep out of reach of children. In case of overdose, get medical help or contact a Poison Control Center right away.

Do not use if tamper evident seal is broken or missing.

Store in cool, dry place.

Keep out of reach of children. In case of overdose, get medical help or contact a Poison Control Center right away.

DIRECTIONS:

Shake well before use. Adults: 3 sprays orally, once daily or as directed by a health care professional.

INDICATIONS:

For the temporary relief of numbness, tingling, trembling, paralysis, short of breath, burning eyes.

INACTIVE INGREDIENTS:

Citric Acid, Demineralized Water, eTHANOL 5%, Glycerin, Sodium Benzoate.

QUESTIONS:

Distributed by:

BioActive Nutritional, Inc.

1803 N. Wickham Rd.

Melbourne, FL 32935

bioactivenutritional.com

PACKAGE LABEL DISPLAY:

BIOActive Nutritional

BIO CHEM DETOX

HOMEOPATHIC

1 FL OZ (30 ml)